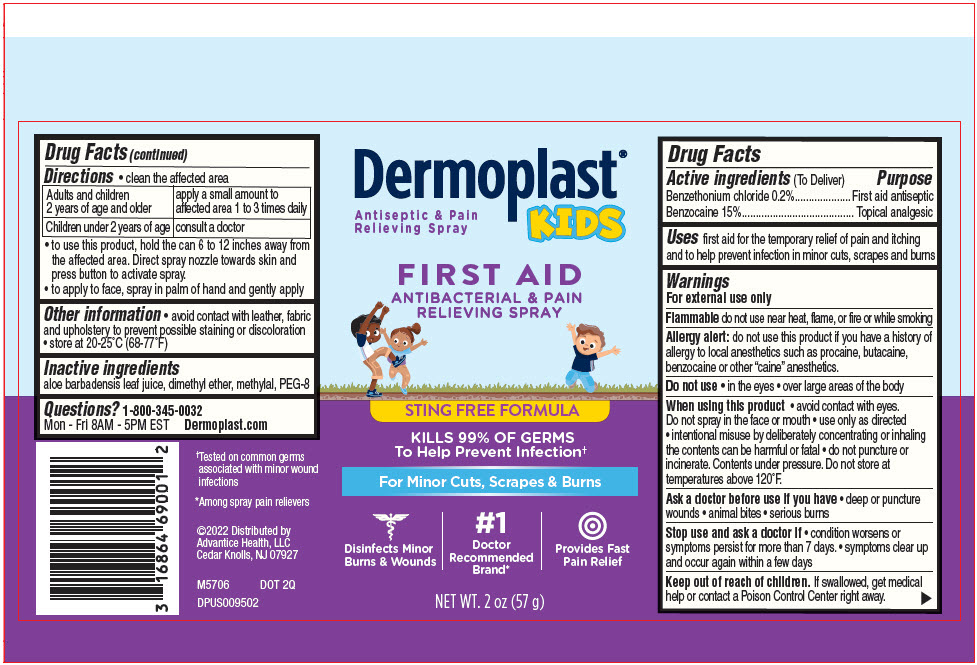 DRUG LABEL: Dermoplast Kids
NDC: 16864-660 | Form: SPRAY
Manufacturer: Advantice Health, LLC.
Category: otc | Type: HUMAN OTC DRUG LABEL
Date: 20241212

ACTIVE INGREDIENTS: BENZETHONIUM CHLORIDE 2 mg/1 g; BENZOCAINE 150 mg/1 g
INACTIVE INGREDIENTS: POLYETHYLENE GLYCOL 400; METHYLAL; ALOE VERA LEAF; DIMETHYL ETHER

Dermoplast®Kids
First Aid Spray

Drug Facts

ACTIVE INGREDIENT

Active ingredients(To Deliver) | Purpose
Benzethonium chloride 0.2% | First aid antiseptic
Benzocaine 15% | Topical analgesic

Uses

first aid for the temporary relief of pain and itching and to help prevent infection in minor cuts, scrapes and burns

Warnings

For external use only

Flammabledo not use near heat, flame, or fire or while smoking

Allergy alert:do not use this product if you have a history of allergy to local anesthetics such as procaine, butacaine, benzocaine or other "caine" anesthetics.

Do not use

- in the eyes
- over large areas of the body

When using this product

- avoid contact with eyes. Do not spray in the face or mouth
- use only as directed
- intentional misuse by deliberately concentrating or inhaling the contents can be harmful or fatal
- do not puncture or incinerate. Contents under pressure. Do not store at temperatures above 120°F.

Ask a doctor before use if you have

- deep or puncture wounds
- animal bites
- serious burns

Stop use and ask a doctor if

- condition worsens or symptoms persist for more than 7 days.
- symptoms clear up and occur again within a few days

Keep out of reach of children.If swallowed, get medical help or contact a Poison Control Center right away.

Directions

- clean the affected area

Adults and children 2 years of age and older | apply a small amount to affected area 1 to 3 times daily
Children under 2 years of age | consult a doctor

- to use this product, hold the can 6 to 12 inches away from the affected area. Direct spray nozzle towards skin and press button to activate spray.
- to apply to face, spray in palm of hand and gently apply

Other information

- avoid contact with leather, fabric and upholstery to prevent possible staining or discoloration
- store at 20-25°C (68-77°F)

Inactive ingredients

aloe barbadensis leaf juice, dimethyl ether, methylal, PEG-8

Questions?

1-800-345-0032

Mon - Fri 8AM - 5PM EST
Dermoplast.com

Distributed by
Advantice Health, LLC
Cedar Knolls, NJ 07927

PRINCIPAL DISPLAY PANEL - 57 g Can Label

Dermoplast®
KIDS

Antiseptic & Pain
Relieving Spray

FIRST AID
ANTIBACTERIAL & PAIN
RELIEVING SPRAY

STING FREE FORMULA

KILLS 99% OF GERMS
To Help Prevent Infection†

For Minor Cuts, Scrapes & Burns

Disinfects Minor
Burns & Wounds

#1
Doctor
Recommended
Brand*

Provides Fast
Pain Relief

NET WT. 2 oz (57 g)